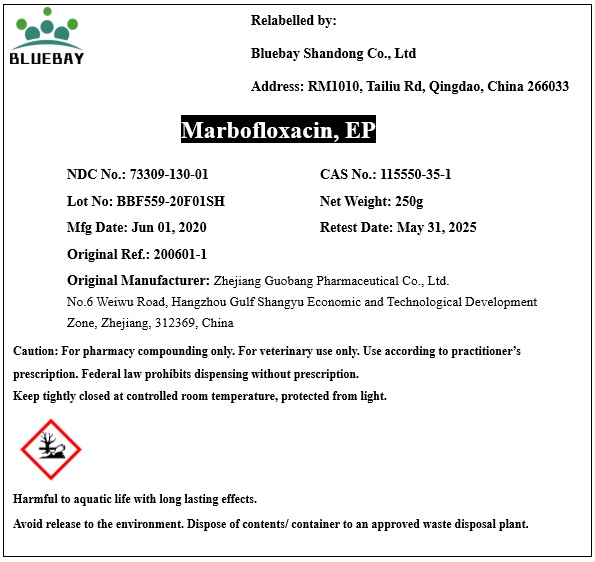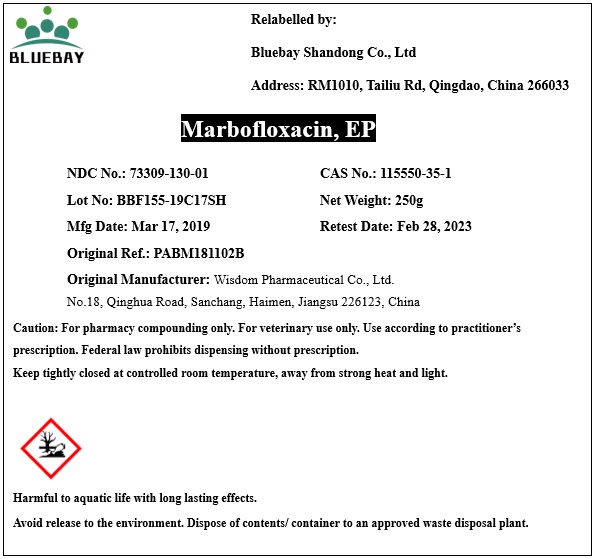 DRUG LABEL: Marbofloxacin
NDC: 73309-130 | Form: POWDER
Manufacturer: BLUEBAY SHANDONG CO.,LTD
Category: other | Type: BULK INGREDIENT
Date: 20201119

ACTIVE INGREDIENTS: MARBOFLOXACIN 1 g/1 g

Marbofloxacin